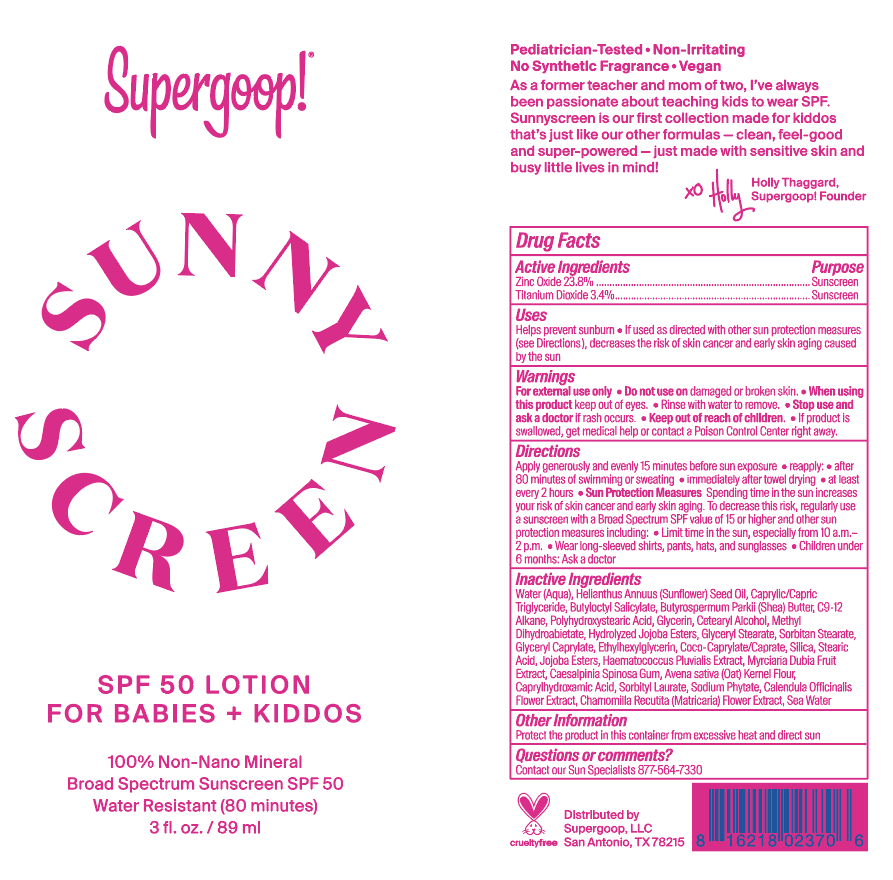 DRUG LABEL: Sunnyscreen SPF 50
NDC: 75936-250 | Form: LOTION
Manufacturer: Supergoop, LLC
Category: otc | Type: HUMAN OTC DRUG LABEL
Date: 20231214

ACTIVE INGREDIENTS: TITANIUM DIOXIDE 3.4 g/100 mL; ZINC OXIDE 23.8 g/100 mL
INACTIVE INGREDIENTS: METHYL DIHYDROABIETATE; MYRCIARIA DUBIA FRUIT; POLYHYDROXYSTEARIC ACID (2300 MW); PHYTATE SODIUM; SORBITYL LAURATE; BUTYLOCTYL SALICYLATE; CAESALPINIA SPINOSA RESIN; MEDIUM-CHAIN TRIGLYCERIDES; COCO-CAPRYLATE/CAPRATE; SHEA BUTTER; HYDROLYZED JOJOBA ESTERS (ACID FORM); PROPANEDIOL; SODIUM CHLORIDE; GLYCERYL CAPRYLATE; SILICON DIOXIDE; STEARIC ACID; WATER; OATMEAL; CALENDULA OFFICINALIS FLOWER; CAPRYLHYDROXAMIC ACID; CHAMOMILE; CETOSTEARYL ALCOHOL; GLYCERYL MONOSTEARATE; SORBITAN MONOSTEARATE; ETHYLHEXYLGLYCERIN; GLYCERIN; HAEMATOCOCCUS PLUVIALIS; SUNFLOWER OIL

Sunnyscreen SPF Lotion of Babies + kiddos

Active Ingredients Purpose

TItanium Dioxide 3.4% Sunscreen

Zinc Oxide 23.8% Sunscreen

Uses

- Helps Prevent Sunburn
- If used as directed with other sun protection measures (see Directions), decreases the risk of skin cancer and early skin aging caused by the sun.

Keep out of reach of children

If product is swallowed, get medical help or contact a poison Control Center right away

Stop use and ask a doctor if rash occurs or irritation develops and lasts.

Warnings

Do not use on damaged or broken skin

When using this product keep out of eyes. Rinse with water to remove

For external use only

Directions

- Apply liberally and generously 15 minutes before sun exposure.
- Reapply:
- after 80 minutes of swimming or sweating
- immediately after towel drying
- at least every 2 hours.
- Sun Protection Measures Spending time in the sun increases your risk of

skin cancer and early skin aging. To decrease this risk, regularly use a
sunscreen with a Broad Spectrum SPF value of 15 or higher and other sun
protection measures including:

- limit your time in the sun, especially from 10

a.m. – 2 p.m.

- wear long-sleeved shirts, pants, hats, and sunglasses
- Children under 6 months of age: ask a doctor.

INACTIVE INGREDIENT

Avena Sativa (Oat) Kernel Flour, Butyloctyl Salicylate, Butyrospermum Parkii (Shea) Butter, C9-12 Alkane, Caesalpinia Spinosa Gum, Calendula Officinalis Flower Extract, Caprylhydroxamic Acid, Caprylic/Capric Triglyceride,Cetearyl Alcohol,Chamomila Recutita (Matricaria) Flower Extract, Coco-Caprylate/Caprate, Ethylhexylglycerin, Glycerin, Glyceryl Caprylate, Glyceryl Stearate, Haematococcus Pluvialis Extract, Helianthus Annuus (Sunflower) Seed Oil, Hydrolyzed Jojoba Esters, Jojoba Esters, Methyl Dihydroabietate, Myrciaria Dubia Fruit Extract, Polyhydroxystearic Acid, Propanediol, Sea Water, Silica, Sodium Phytate, Sorbitan Stearate, Sorbityl Laurate, Stearic Acid, Water

PACKAGE LABEL

Sunnyscreen SPF 50 Lotion for babies+ Kiddos

3 fl. oz./ 89 ml